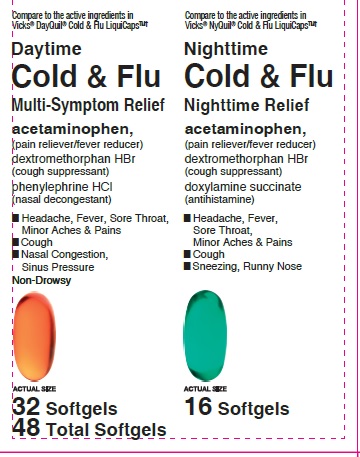 DRUG LABEL: Daytime Nighttime Cold and Flu
NDC: 85828-695 | Form: KIT | Route: ORAL
Manufacturer: Grocery Outlet, Inc.
Category: otc | Type: HUMAN OTC DRUG LABEL
Date: 20251126

ACTIVE INGREDIENTS: ACETAMINOPHEN 325 mg/1 1; PHENYLEPHRINE HYDROCHLORIDE 5 mg/1 1; DEXTROMETHORPHAN HYDROBROMIDE 10 mg/1 1; ACETAMINOPHEN 325 mg/1 1; DOXYLAMINE SUCCINATE 6.25 mg/1 1; DEXTROMETHORPHAN HYDROBROMIDE 15 mg/1 1
INACTIVE INGREDIENTS: SHELLAC; FD&C RED NO. 40; GELATIN; POLYETHYLENE GLYCOL, UNSPECIFIED; FD&C YELLOW NO. 6; GLYCERIN; POVIDONE; TITANIUM DIOXIDE; PROPYLENE GLYCOL; WATER; SORBITOL SOLUTION; SORBITAN; SHELLAC; FD&C BLUE NO. 1; GELATIN; D&C YELLOW NO. 10; GLYCERIN; POLYETHYLENE GLYCOL, UNSPECIFIED; POVIDONE; TITANIUM DIOXIDE; WATER; SORBITOL SOLUTION; PROPYLENE GLYCOL; SORBITAN

Grocery Outlet Daytime and Nighttime Cold & Flu Softgels

Active ingredients (in each softgel)
Acetaminophen 325 mg
Dextromethorphan HBr 10 mg
Phenylephrine HCl 5 mg

Purpose

Pain reliever/ Fever reducer

Cough suppressant

Nasal decongestant

Uses

temporarily relieves common cold/flu symptoms:

- nasal congestion
- cough due to minor throat & bronchial irritation
- sore throat
- headache
- minor aches & pains
- fever

Warnings

Liver warning:This product contains acetaminophen. Severe liver damage may occur if you take

- more than 4 doses in 24 hrs, which is the maximum daily amount for this product
- with other drugs containing acetaminophen
- 3 or more alcoholic drinks every day while using this product

Allergy alert:Acetaminophen may cause severe skin reactions. Symptoms may include:

- skin reddening
- blisters
- rash

If a skin reaction occurs, stop use and seek medical help right away.

Sore throat warning:If sore throat is severe, persists for more than 2 days, is accompanied or followed by fever, headache, rash, nausea, or vomiting, consult a doctor promptly.

Do not use

- with any other drug containing acetaminophen (prescription or nonprescription). If you are not sure whether a drug contains acetaminophen, ask a doctor or pharmacist.
- if you are now taking a prescription monoamine oxidase inhibitor (MAOI) (certain drugs for depression, psychiatric or emotional conditions, or Parkinson's disease), or for 2 weeks after stopping the MAOI drug. If you do not know if your prescription drug contains an MAOI, ask a doctor or pharmacist before taking this product.

Ask a doctor before use if you have

- liver disease
- heart disease
- high blood pressure
- thyroid disease
- diabetes
- trouble urinating due to enlarged prostate gland
- cough that occurs with too much phlegm (mucus)
- persistent or chronic cough such as occurs with smoking, asthma, or emphysema

Ask a doctor or pharmacist before use if you aretaking the blood thinning drug warfarin.

When using this product, do not use more than directed.

Stop use and ask a doctor if

- you get nervous, dizzy or sleepless
- pain, nasal congestion or cough get worse or last more than 7 days
- fever gets worse or lasts more than 3 days
- redness or swelling is present
- new symptoms occur
- cough comes back, or occurs with rash or headache that lasts.

These could be signs of a serious condition.

PREGNANCY OR BREAST FEEDING

If pregnant or breastfeeding,ask a health professional before use.

Keep out of reach of children.In case of overdose, get medical help or contact a Poison Control Center (1-800-222-1222) right away. Quick medical attention is critical for adults & for children even if you do not notice any signs or symptoms.

Directions

- take only as directed
- do not exceed 4 doses per 24 hrs

adults & children 12 yrs & over | 2 softgels with water every 4 hrs
children 4 to under 12 yrs | ask a doctor
children under 4 yrs | do not use

Other information

- store at room temperature

INACTIVE INGREDIENT

Inactive ingredientsFD&C red#40, FD&C yellow #6, gelatin, glycerin, polyethylene glycol, povidone, propylene glycol, purified water, shellac, sorbitol sorbitan solution, titanium dioxide.

Questions or comments?Call 1-877-290-4008

Active ingredients (in each softgel)

Acetaminophen 325 mg

Dextromethorphan HBr 15 mg

Doxylamine succinate 6.25 mg

Purpose

Pain reliever/Fever reducer

Cough suppressant

Antihistamine

Uses

temporarily relieves common cold/flu symptoms:

- cough due to minor throat & bronchial irritation
- sore throat
- headache
- minor aches & pains
- fever
- runny nose & sneezing

Warnings

Liver warning:This product contains acetaminophen. Severe liver damage may occur if you take

- more than 4 doses in 24 hrs, which is the maximum daily amount for this product
- with other drugs containing acetaminophen
- 3 or more alcoholic drinks every day while using this product

Allergy alert:Acetaminophen may cause severe skin reactions. Symptoms may include:

- skin reddening
- blisters
- rash

If a skin reaction occurs, stop use and seek medical help right away.

Sore throat warning:If sore throat is severe, persists for more than 2 days, is accompanied or followed by fever, headache, rash, nausea, or vomiting, consult a doctor promptly.

Do not use

- with any other drug containing acetaminophen (prescription or nonprescription). If you are not sure whether a drug contains acetaminophen, ask a doctor or pharmacist.
- if you are now taking a prescription monoamine oxidase inhibitor (MAOI) (certain drugs for depression, psychiatric or emotional conditions, or Parkinson's disease), or for 2 weeks after stopping the MAOI drug. If you do not know if your prescription drug contains an MAOI, ask a doctor or pharmacist before taking this product.

Ask a doctor before use if you have

- liver disease
- glaucoma
- cough that occurs with too much phlegm (mucus)
- a breathing problem or chronic cough that lasts or as occurs with smoking, asthma, chronic bronchitis or emphysema
- trouble urinating due to enlarged prostate gland

Ask a doctor or pharmacist before use if you are

- taking sedatives or tranquilizers
- taking the blood thinning drug warfarin

When using this product

- excitability may occur, especially in children
- marked drowsiness may occur
- avoid alcoholic drinks
- be careful when driving a motor vehicle or operating machinery
- alcohol, sedatives, & tranquilizers may increase drowsiness

Stop use and ask a doctor if

- pain or cough gets worse or lasts more than 7 days
- fever gets worse or lasts more than 3 days
- redness or swelling is present
- new symptoms occur
- cough comes back or occurs with rash or headache that lasts.

These could be signs of a serious condition.

PREGNANCY OR BREAST FEEDING

If pregnant or breastfeeding,ask a health professional before use.

Keep out of reach of children.In case of overdose, get medical help or contact a Poison Control Center (1-800-222-1222) right away. Quick medical attention is critical for adults as well as for children even if you do not notice any signs or symptoms.

Directions

- take only as directed
- do not exceed 4 doses per 24 hours

adults & children 12 yrs & over | 2 softgels with water every 6 hrs
children 4 to under 12 yrs | ask a doctor
children under 4 yrs | do not use

Other information

- store at room temperature

INACTIVE INGREDIENT

Inactive ingredientsD&C yellow #10, FD&C blue #1, gelatin, glycerin, polyethylene glycol, povidone, propylene glycol, purified water, shellac, sorbitol sorbitan solution, titanium dioxide.

Questions or comments?Call 1-877-290-4008